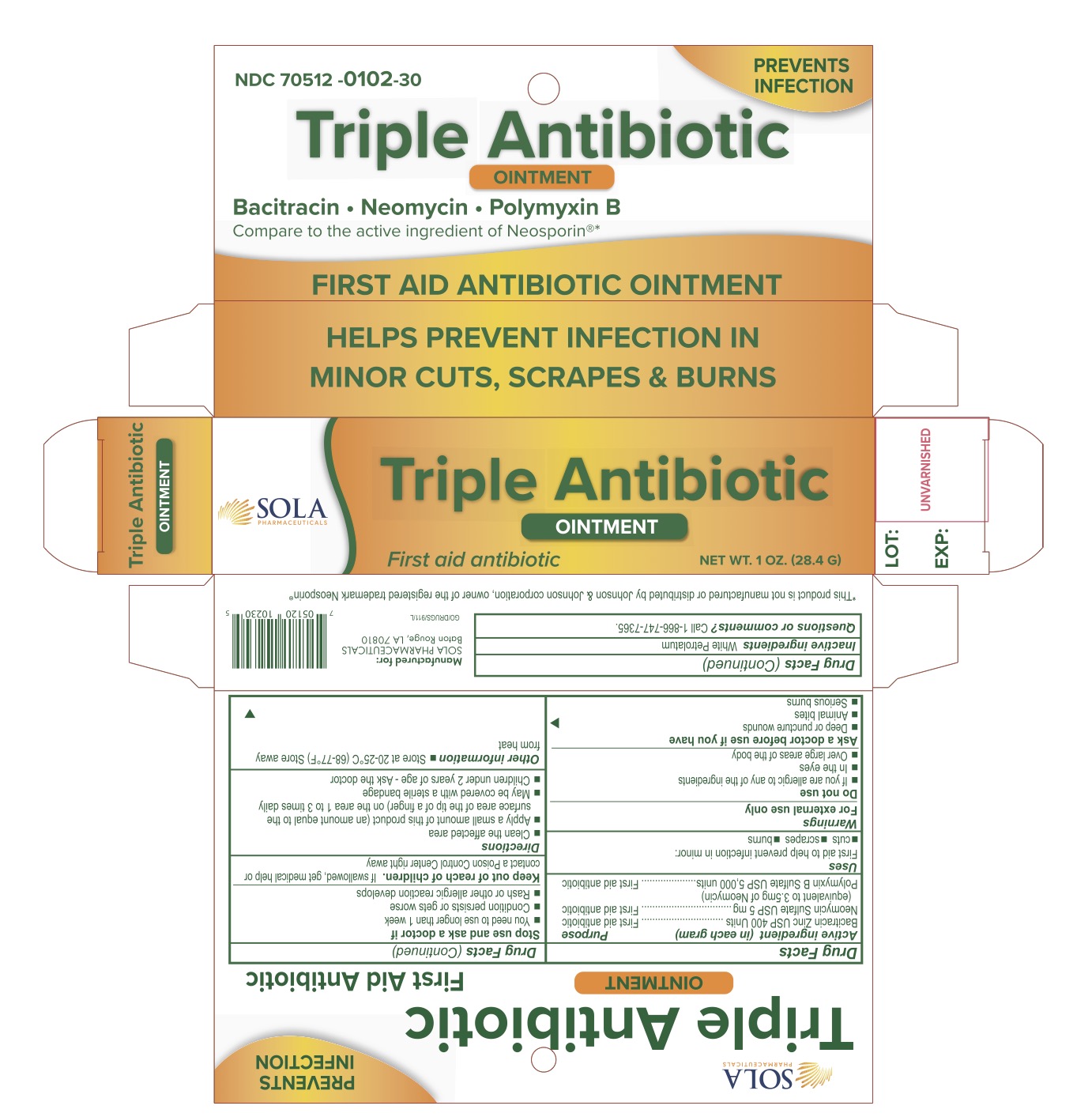 DRUG LABEL: Triple Antibiotic
NDC: 70512-102 | Form: OINTMENT
Manufacturer: SOLA Pharmaceuticals
Category: otc | Type: HUMAN OTC DRUG LABEL
Date: 20220705

ACTIVE INGREDIENTS: NEOMYCIN SULFATE 5 mg/1 g; POLYMYXIN B SULFATE 5000 [USP'U]/1 g; BACITRACIN ZINC 400 [USP'U]/1 g
INACTIVE INGREDIENTS: WHITE PETROLATUM

Triple Antibiotic Ointment

Active Ingerdients (in each gram)

Bacitracin Zinc USP 400 Units

Neomycin Sulfate USP 5mg (equivalent to 3.5mg of Neomycin)

Polymixin B Sulfate USP 5,000 Units

Purpose

First aid antibiotic

Uses

First aid to help prevent infection in minor:

- cuts
- scrapes
- burns

Warnings

For external use only

Do not use:

- If you are allergic to any of the ingredients
- In the eyes
- Over large areas of the body

Ask a doctor before use if you have

- Deep or puncture wounds
- Animal bites
- Serious burns

Stop use and ask a doctor if:

- You need to use longer than 1 week
- Condition persists or gets worse
- Rash or other allergic reaction developes

Keep out of reach of children.

If swallowed, get medical help or contact a Poison Control Center right away

Directions

- Clean the affected area
- Apply a small amount of this product (an amount equal to the surface area of the tip of a finger) on the area 1 to 3 times daily
- May be covered with a sterile bandage
- Children under 2 years of age - Ask the doctor

Other Information

- Store at 20-25°C (68-77°F)
- Store away from heat

Inactive ingredients

White Petrolatum

Questions or comments?

Call 1-866-747-7365

PACKAGE LABEL

Manufactured for : SOLA Pharmaceuticals
Baton Rouge, LA 70810

Triple Antibiotic

NDC 70512-102-30

Qty: 28.4g